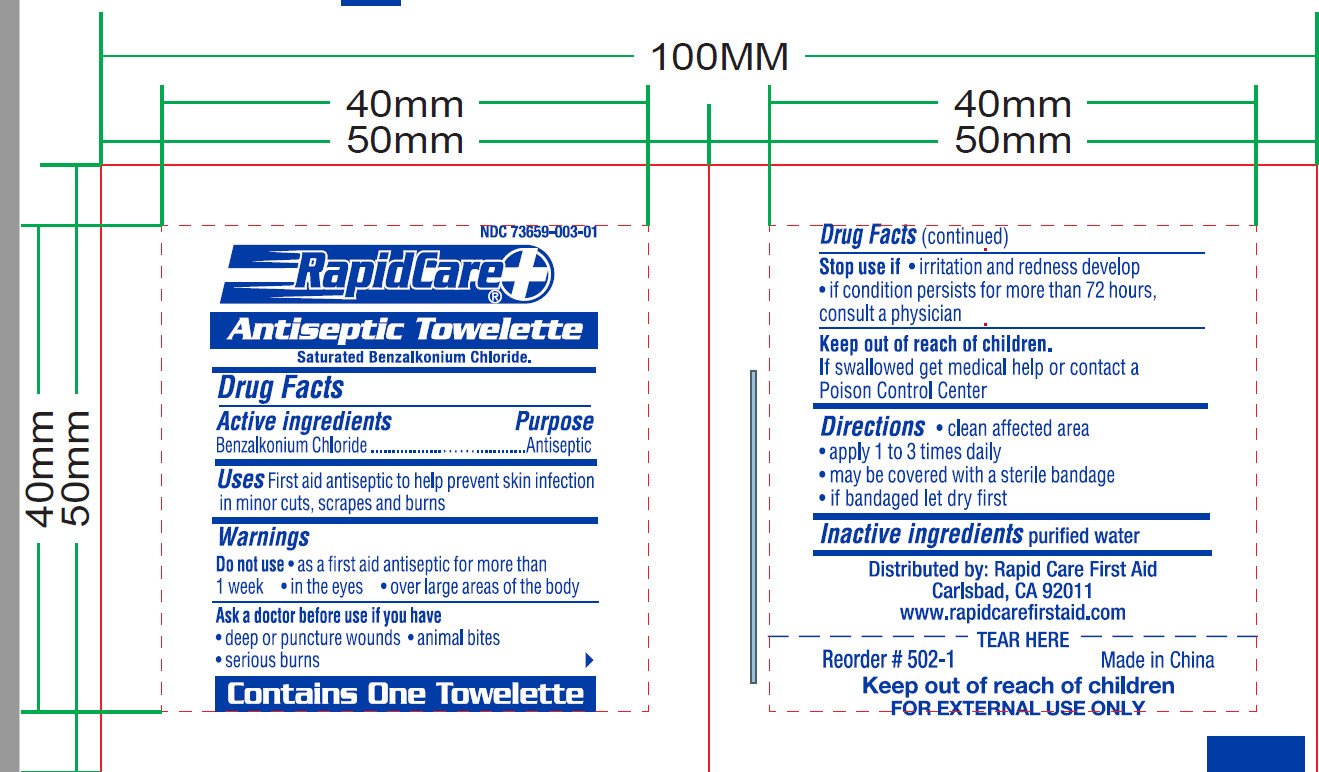 DRUG LABEL: BZK Pad
NDC: 72766-008 | Form: SWAB
Manufacturer: Yangzhou Suxiang Medical Instrument Co., Ltd.
Category: otc | Type: HUMAN OTC DRUG LABEL
Date: 20210331

ACTIVE INGREDIENTS: BENZALKONIUM CHLORIDE 0.13 g/1 1
INACTIVE INGREDIENTS: WATER

ACTIVE INGREDIENT

Benzalkonium Chloride

PURPOSE

Antiseptic

USE

First aid antiseptic to help prevent skin infection in minor cuts, scrapes and burns

WARNINGS

For external use only

DO NOT USE

as a first aid antiseptic for more than 1 week
in the eyes
over large areas of the body

ASK DOCTOR

deep or puncture wounds
animal bites
serious burns

STOP USE

irritation and redness develop
if condition persists for more than 72 hours, consult a physician

DO NOT USE

If swallowed get medical help or contact a Poison Control right away.

DIRECTIONS

clean affected area
apply 1 to 3 times daily
may be covered with a sterile bandage
if bandaged let dry first

OTHER INFORMATION

stor at room temperaturel15°-30° C (59°-86° F)

INACTIVE INGREDIENT

purified water

keep out of reach of children